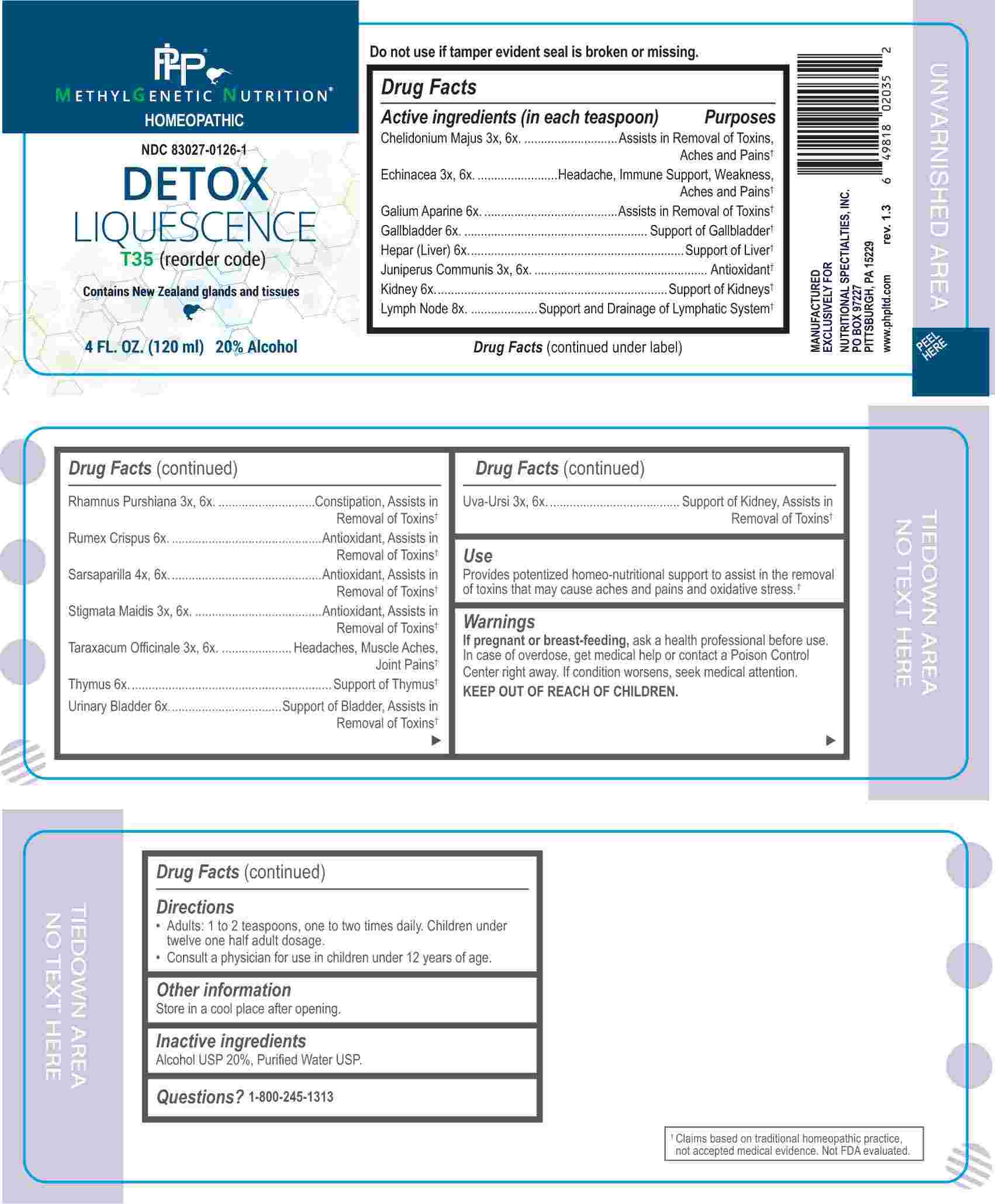 DRUG LABEL: Detox Liquescence
NDC: 83027-0126 | Form: LIQUID
Manufacturer: Nutritional Specialties, Inc.
Category: homeopathic | Type: HUMAN OTC DRUG LABEL
Date: 20240903

ACTIVE INGREDIENTS: CHELIDONIUM MAJUS WHOLE 3 [hp_X]/1 mL; ECHINACEA ANGUSTIFOLIA WHOLE 3 [hp_X]/1 mL; JUNIPER BERRY 3 [hp_X]/1 mL; FRANGULA PURSHIANA BARK 3 [hp_X]/1 mL; CORN SILK 3 [hp_X]/1 mL; TARAXACUM OFFICINALE 3 [hp_X]/1 mL; ARCTOSTAPHYLOS UVA-URSI LEAF 3 [hp_X]/1 mL; SMILAX ORNATA ROOT 4 [hp_X]/1 mL; GALIUM APARINE WHOLE 6 [hp_X]/1 mL; BOS TAURUS GALLBLADDER 6 [hp_X]/1 mL; BEEF LIVER 6 [hp_X]/1 mL; BEEF KIDNEY 6 [hp_X]/1 mL; RUMEX CRISPUS ROOT 6 [hp_X]/1 mL; LAMB 6 [hp_X]/1 mL; SUS SCROFA URINARY BLADDER 6 [hp_X]/1 mL; SUS SCROFA LYMPH 8 [hp_X]/1 mL
INACTIVE INGREDIENTS: WATER; ALCOHOL

DRUG FACTS:

ACTIVE INGREDIENTS:

(in each teaspoon) Chelidonium Majus 3X, 6X, Echinacea 3X, 6X, Galium Aparine 6X, Gallbladder 6X, Hepar (Liver) 6X, Juniperus Communis 3X, 6X, Kidney 6X, Lymph Node 8X, Rhamnus Purshiana 3X, 6X, Rumex Crispus 6X, Sarsaparilla 4X, 6X, Stigmata Maidis 3X, 6X, Taraxacum Officinale 3X, 6X, Thymus 6X, Urinary Bladder 6X, Uva-Ursi 3X, 6X.

PURPOSE:

Chelidonium Majus – Assists in Removal of Toxins, Aches and Pains,† Echinacea – Headache, Immune Support, Weakness, Aches and Pains,† Galium Aparine – Assists in Removal of Toxins,† Gallbladder – Support of Gallbladder,† Hepar (Liver) – Support of Liver,† Juniperus Communis - Antioxidant,† Kidney – Support of Kidneys,† Lymph Node – Support and Drainage of Lymphatic System,† Rhamnus Purshiana – Constipation, Assists in Removal of Toxins,† Rumex Crispus – Antioxidant, Assists in Removal of Toxins,† Sarsaparilla – Antioxidant, Assists in Removal of Toxins,† Stigmata Maidis – Antioxidant, Assists in Removal of Toxins,† Taraxacum Officinale – Headaches, Muscle Aches, Joint Pains,† Thymus – Support of Thymus,† Urinary Bladder – Support of Bladder, Assists in Removal of Toxins,† Uva-Ursi – Support of Kidney, Assists in Removal of Toxins†

USES:

Provides potentized homeo-nutritional support to assist in the removal of toxins that may cause aches and pains and oxidative stress.†

†Claims based on traditional homeopathic practice, not accepted medical evidence. Not FDA evaluated.

WARNINGS:

If pregnant or breast-feeding, ask a health professional before use.

In case of overdose, get medical help or contact a Poison Control Center right away.

If condition worsens, seek medical attention.

KEEP OUT OF REACH OF CHILDREN

Do not use if tamper evident seal is broken or missing.

Store in a cool place after opening

KEEP OUT OF REACH OF CHILDREN:

In case of overdose, get medical help or contact a Poison Control Center right away.

DIRECTIONS:

• Adults: 1 to 2 teaspoons, one to two times daily. Children under twelve one half adult dosage.

• Consult a physician for use in children under 12 years of age.

INACTIVE INGREDIENTS:

Alcohol USP 20%, Purified Water USP.

QUESTIONS:

MANUFACTURED EXCLUSIVELY FOR

NUTRITIONAL SPECIALTIES, INC.

PO BOX 97227

PITTSBURG, PA 15229

www.phpltd.com

PACKAGE LABEL DISPLAY:

METHYLGENETIC NUTRITION

HOMEOPATHIC

NDC 83027-0126-1

DETOX

LIQUESCENCE

4 FL.OZ.